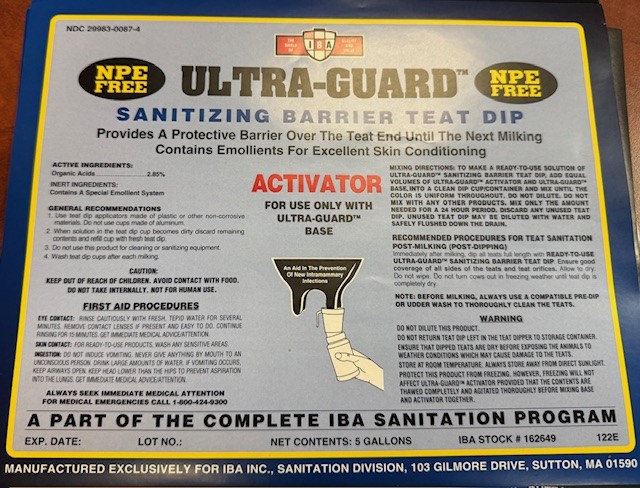 DRUG LABEL: ULTRA-GUARD ACTIVATOR
NDC: 29983-0087 | Form: SOLUTION
Manufacturer: IBA
Category: animal | Type: OTC ANIMAL DRUG LABEL
Date: 20241226

ACTIVE INGREDIENTS: LACTIC ACID 28.5 g/1 L
INACTIVE INGREDIENTS: SODIUM HYDROXIDE; UREA

ULTRA-GUARD SANITIZING BARRIER TEAT DIP PROVIDES A PROTECTIVE BARRIER OVER THE TEAT END UNTIL THE NEXT MILKING CONTAINS EMOLLIENTS FOR EXCELLENT SKIN CONDITIONING

ACTIVE INGREDIENT

Organic Acids...........2.85%

INERT INGREDIENTS
Contains A Special Emollient System

INDICATIONS AND USAGE

GENERAL RECOMMENDATIONS

To make a ready-to-use solution of Ultra-Guard Sanitizing Barrier Teat dip, add equal volumes of Ultra-Guard Activator and Ultra-Guard Base into a clean dip cup/container and mix until the color is uniform throughout. Do not dilute. Mix only the amount needed for one milking of the herd. Discard any unused teat dip. Do not mix with any other products.

RECOMMENDED PROCEDURES FOR TEAT SANITATION
POST-MILKING (POST-DIPPING)
Immediately after milking, dip all teats full length with READY-TO-USE ULTRA-GUARD SANITIZING BARRIER TEAT DIP. Ensure good coverage of all sides of the teats and teat orifices. Allow to dry. Do not wipe. Do not turn cows out in freezing weather until teat dip is completely dry.

NOTE: Before milking, use a compatible teat dip or udder wash to thoroughly clean the teats.

WARNING

Do not dilute this product.
Do not return teat dip left in the teat dipper to storage container.
Ensure that dipped teats are dry before exposing the animals to weather conditions which may cause damage to the teats.
Store at room temperature. Always store away from direct sunlight.

Protect this product from freezing. However, freezing will not affect ULTRA-GUARD ACTIVATOR provided that the contents are thawed completely and agitated thoroughly before mixing base and activator together.

CAUTION: KEEP OUT OF REACH OF CHILDREN.
AVOID CONTACT WITH FOOD. DO NOT TAKE INTERNALLY.

FIRST AID PROCEDURES

EYE CONTACT: Rinse cautiously with fresh, tepid water for several minutes. Remove contact lenses if present and easy to do. Continue rinsing for 15 minutes. Get immediate medical advice/attention. SKIN CONTACT: For RTU products wash any sensitive areas. INGESTION: Do not induce vomiting. Never give anything by mouth to an unconscious person. Drink large amounts of water. If vomiting occurs, keep airways open. Keep head lower than the hips to prevent aspiration into the lungs. Get immediate medical advice/attention.

ALWAYS SEEK IMMEDIATE MEDICAL ATTENTION

FOR MEDICAL EMERGENCIES CALL 1-800-424-9300